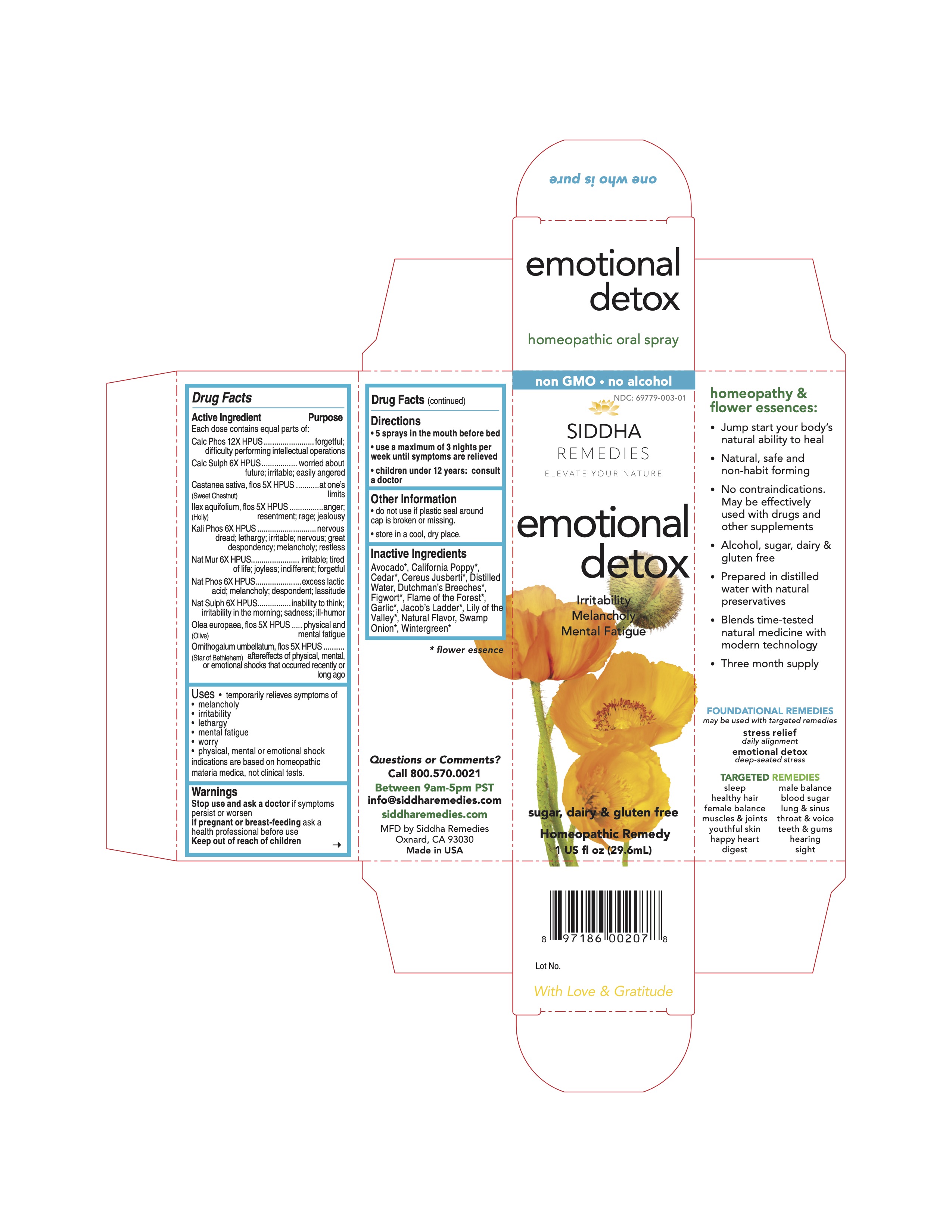 DRUG LABEL: emotional detox
NDC: 69779-003 | Form: SPRAY
Manufacturer: Siddha Flower Essences LLC
Category: homeopathic | Type: HUMAN OTC DRUG LABEL
Date: 20251231

ACTIVE INGREDIENTS: TRIBASIC CALCIUM PHOSPHATE 12 [hp_X]/29.6 mL; CALCIUM SULFATE ANHYDROUS 6 [hp_X]/29.6 mL; CASTANEA SATIVA FLOWER 5 [hp_X]/29.6 mL; ILEX AQUIFOLIUM FLOWERING TOP 5 [hp_X]/29.6 mL; POTASSIUM PHOSPHATE, DIBASIC 6 [hp_X]/29.6 mL; SODIUM CHLORIDE 6 [hp_X]/29.6 mL; SODIUM PHOSPHATE, DIBASIC, HEPTAHYDRATE 6 [hp_X]/29.6 mL; SODIUM SULFATE 6 [hp_X]/29.6 mL; OLEA EUROPAEA FLOWER 5 [hp_X]/29.6 mL; ORNITHOGALUM UMBELLATUM FLOWERING TOP 5 [hp_X]/29.6 mL
INACTIVE INGREDIENTS: AVOCADO; ESCHSCHOLZIA CALIFORNICA FLOWERING TOP; LAMPROCAPNOS SPECTABILIS FLOWER; SCROPHULARIA NODOSA; BUTEA MONOSPERMA FLOWER; GARLIC; LINARIA VULGARIS; CONVALLARIA MAJALIS FLOWERING TOP; WATER; GAULTHERIA PROCUMBENS TOP

Drug Facts

Active Ingredient

Each dose contains equal parts of:
Cal Phos 12X HPUS
Calc Sulph 6X HPUS
Castanea sativa, flos (Sweet Chestnut) 5X HPUS
Ilex aquifolium, flos (Holly) 5X HPUS
Kali Phos 6X HPUS
Nat Mur 6X HPUS
Nat Phos 6X HPUS
Nat Sulph 6X HPUS
Olea europaea, flos (Olive) 5X HPUS
Ornithogalum umbellatum, flos (Star of Bethlehem) 5X HPUS

Purpose

Each dose contains equal parts of:
Cal Phos 12X HPUS................................................................forgetful, difficulty performing intellectual operations
Calc Sulph 6X HPUS...............................................................worried about future; irritable; easily angered
Castanea sativa, flos (Sweet Chestnut) 5X HPUS......................at one's limits
Ilex aquifolium, flos (Holly) 5X HPUS........................................anger; resentment; rage; jealousy
Kali Phos 6X HPUS................................................................nervous; dread; lethargy; irritable; nervous; great despondency; melancholy; restless
Nat Mur 6X HPUS...................................................................irritable; tired of life; joyless; indifferent; forgetful
Nat Phos 6X HPUS.................................................................excessive lactic acid; melancholy; despondent; lassitude
Nat Sulph 6X HPUS.................................................................inability to think; irritability in the morning; sadness; ill-humor
Olea europaea, flos (Olive) 5X HPUS........................................physical and mental fatigue
Ornithogalum umbellatum, flos (Star of Bethlehem) 5X HPUS.....aftereffects of physical, mental, or emotional shocks that occurred recently or long ago

Uses

- temporarily relives symptoms of
- melancholy
- irritability
- lethargy
- mental fatigue
- worry
- physical, mental or emotional shock

indications are based on homeopathic materia medica, not clinical tests.

Warnings

Stop use and ask a doctor if symptoms persist or worsen

PREGNANCY OR BREAST FEEDING

If pregnant or breast-feeding ask a health professional before use

Keep out of reach of children

Directions

- 5 sprays in mouth before bed
- use a maximum of 3 nights per week until symptoms are relieved
- children under 12 years: consult a doctor

Other Information

- do not use if plastic seal around cap is broken or missing.
- store in a cool, dry place.

Inactive Ingredients

Avocado*, California Poppy*, Cedar*, Cereus Jusberti*, Dutchman's Breeches*, Figwort*, Flame of the Forest*, Garlic*, Jacob's Ladder*, Lily of the Valley*, Natural Flavor, Purified Water, Swamp Onion*, Wintergreen*

*flower essence

Questions or Comments?

Call 800.570.0021
Between 9am-5pm PST
info@siddhaflowers.com
siddhaflowers.com

MFD by Siddha Flower Essences
Oxnard, CA 93030

Made in USA

Side Panel

homeopathy and flower essences:

- Jump start your body's natural ability to heal
- Natural, safe and non-habit forming
- No contraindications. May be effectively used with drugs and other supplements
- Alcohol, sugar, dairy and gluten free
- Prepared in purified water with natural preservatives
- Blends time-tested natural medicine with modern technology
- Three month supply

FOUNDATIONAL REMEDIES

may be used with targeted remedies

stress relief
daily alignment
emotional detox
deep-seated stress

TARGETED REMEDIES

sleep male balance
healthy hair blood sugar
female balance lung and sinus
muscles and joints throat and voice
youthful skin teeth and gums
happy heart hearing
digest sight

Principal Display Panel

100% natural - no alcohol
siddha cell salts + flower essences
emotional detox

Irritability
Melancholy
Mental Fatigue
sugar, dairy and gluten free
Homeopathic Remedy
1 US fl oz (29.6mL)